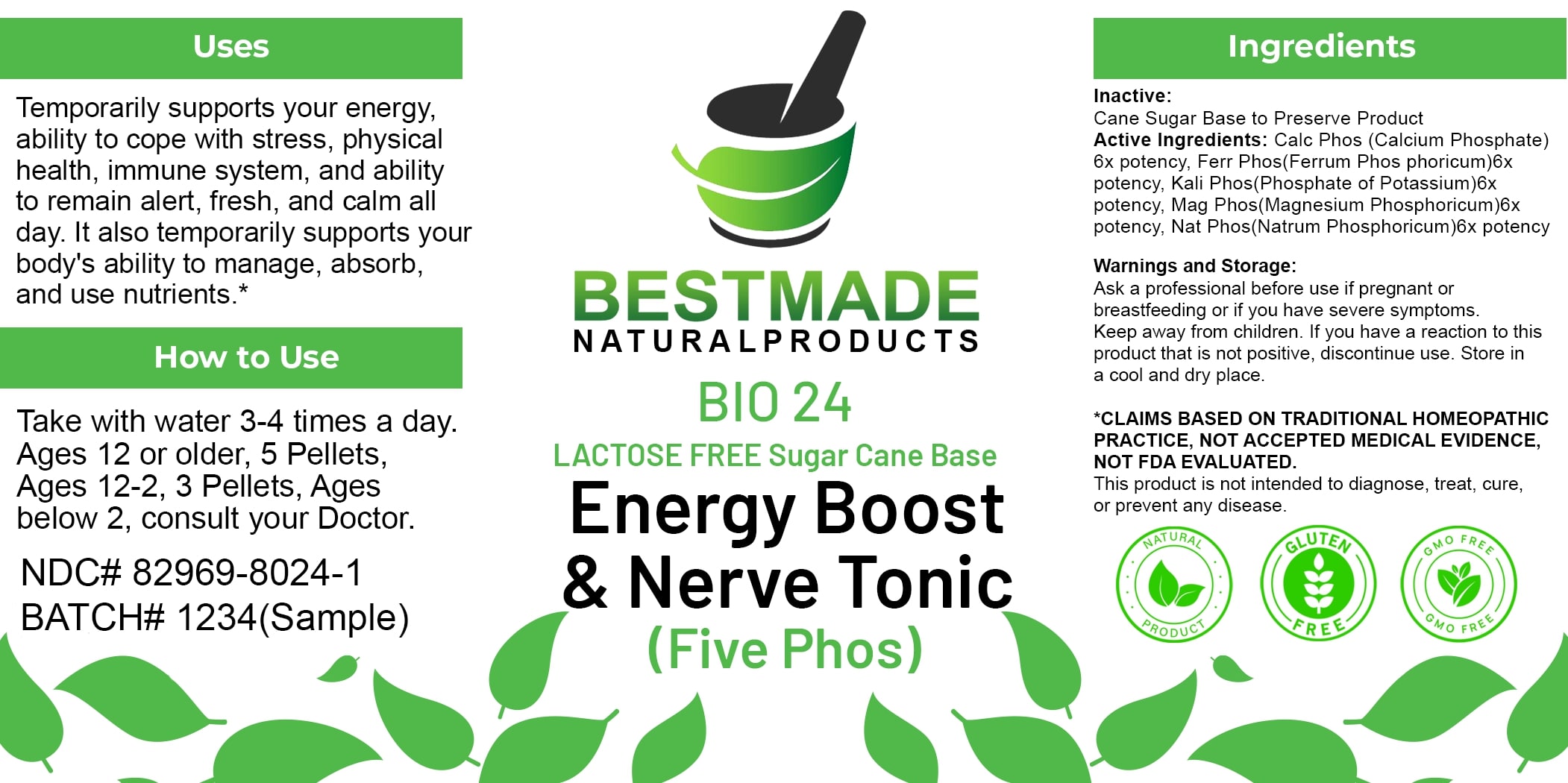 DRUG LABEL: Bestmade Natural Products BIO24 Lactose Free
NDC: 82969-8024 | Form: TABLET, SOLUBLE
Manufacturer: Bestmade Natural Products
Category: homeopathic | Type: HUMAN OTC DRUG LABEL
Date: 20250313

ACTIVE INGREDIENTS: DIBASIC POTASSIUM PHOSPHATE 6 [hp_X]/6 [hp_X]; TRIBASIC CALCIUM PHOSPHATE 6 [hp_X]/6 [hp_X]; FERROSOFERRIC PHOSPHATE 6 [hp_X]/6 [hp_X]; MAGNESIUM PHOSPHATE, DIBASIC TRIHYDRATE 6 [hp_X]/6 [hp_X]; SODIUM PHOSPHATE, DIBASIC, HEPTAHYDRATE 6 [hp_X]/6 [hp_X]
INACTIVE INGREDIENTS: SUCROSE 6 [hp_X]/6 [hp_X]

BIO24 Energy Boost & Nerve Tonic (Five Phos) LACTOSE FREE Sugar Cane Base

DOSAGE AND ADMINISTRATION

How to Use

Take with water 3-4 times a day. Ages 12 or older, 5 Pellets, Ages 12-2, 3 Pellets, Ages below 2, consult your Doctor.

Inactive:

Cane Sugar Base to Preserve Product

Active Ingredients:

Calc Phos (Calcium Phosphate) 6x potency, Ferr Phos (Ferrum Phosphoricum) 6x potency, Kali Phos (Phosphate of Potassium) 6x potency, Mag Phos (Magnesium Phosphoricum) 6x potency, Nat Phos (Natrum Phosphoricum) 6x potency

Uses

Temporarily supports your energy, ability to cope with stress, physical health, immune system, and ability to remain alert, fresh, and calm all day. It also temporarily supports your body's ability to manage, absorb, and use nutrients.*

*CLAIMS BASED ON TRADITIONAL HOMEOPATHIC PRACTICE, NOT ACCEPTED MEDICAL EVIDENCE, NOT FDA EVALUATED.

This product is not intended to diagnose, treat, cure, or prevent any disease.

Uses

Temporarily supports your energy, ability to cope with stress, physical health, immune system, and ability to remain alert, fresh, and calm all day. It also temporarily supports your body's ability to manage, absorb, and use nutrients.*

*CLAIMS BASED ON TRADITIONAL HOMEOPATHIC PRACTICE, NOT ACCEPTED MEDICAL EVIDENCE, NOT FDA EVALUATED.

This product is not intended to diagnose, treat, cure, or prevent any disease.

KEEP OUT OF REACH OF CHILDREN

Warnings and Storage:

Ask a professional before use if pregnant or breastfeeding or if you have severe symptoms. Keep away from children. If you have a reaction to this product that is not positive, discontinue use. Store in a cool and dry place.

Warnings and Storage:

Ask a professional before use if pregnant or breastfeeding or if you have severe symptoms. Keep away from children. If you have a reaction to this product that is not positive, discontinue use. Store in a cool and dry place.

*CLAIMS BASED ON TRADITIONAL HOMEOPATHIC PRACTICE, NOT ACCEPTED MEDICAL EVIDENCE NOT FDA EVALUATED.

This product is not intended to diagnose, treat, cure, or prevent any disease.

Entire package label